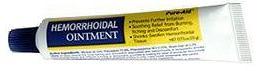 DRUG LABEL: APJ HEMORRHOIDAL
NDC: 46084-111 | Form: OINTMENT
Manufacturer: A P J Laboratories Limited
Category: otc | Type: HUMAN OTC DRUG LABEL
Date: 20130601

ACTIVE INGREDIENTS: PHENYLEPHRINE HYDROCHLORIDE 2.55 mg/1 g; PETROLATUM 720 mg/1 g; MINERAL OIL 140 mg/1 g
INACTIVE INGREDIENTS: PARAFFIN 40 mg/1 g; BUTYLATED HYDROXYTOLUENE 70 mg/1 g; METHYLPARABEN .1 mg/1 g; PROPYLPARABEN .1 mg/1 g; CHLOROCRESOL .02 mg/1 g; LANOLIN .5 mg/1 g; MAGNESIUM STEARATE 1 mg/1 g; LIGHT MINERAL OIL 10 mg/1 g

ACTIVE INGREDIENT

PHENYLEPHRINE HYDROCHLORIDE

PETROLATUM

MINERAL OIL

PURPOSE

Protectant

Vasoconstrictor

KEEP OUT OF REACH OF CHILDREN

If swallowed, get medical help or contact a Poison Control Center right away.

INDICATIONS AND USAGE

■ Helps relieve the local itching and discomfort associated with hemorrhoids.

■ Temporarily shrinks hemorrhoidal tissue and relieves burning.

■ Temporarily provides a coating for relief of anorectal discomforts.

■ Temporarily protects the inflamed, irritated anorectal surface to help make bowel movements less painful.

WARNINGS

For external and/or intrarectal use only

DOSAGE AND ADMINISTRATION

■adults: when practical, cleanse the affected area by patting or blotting with an appropriate cleansing wipe. Gently dry by patting or blotting with a tissue or a soft cloth before applying ointment.

■when first opening the tube, puncture foil seal with top end of cap

■apply to the affected area up to 4 times daily, especially at night, in the morning or after each bowel movement

■intrarectal use:

■remove cover from applicator, attach applicator to tube, lubricate applicator well and gently insert applicator into the rectum

■thoroughly cleanse applicator after each use and replace cover

■also apply ointment to external area

■regular use provides continual therapy for relief of symptoms

■children under 12 years of age: ask a doctor

INACTIVE INGREDIENT

PARAFFIN

BUTYLATED HYDROXYTOLUENE

METHYLPARABEN

PROPYLPARABEN

CHLOROCRESOL

LANOLIN

MAGNESIUM STEARATE

LIGHT MINERAL OIL